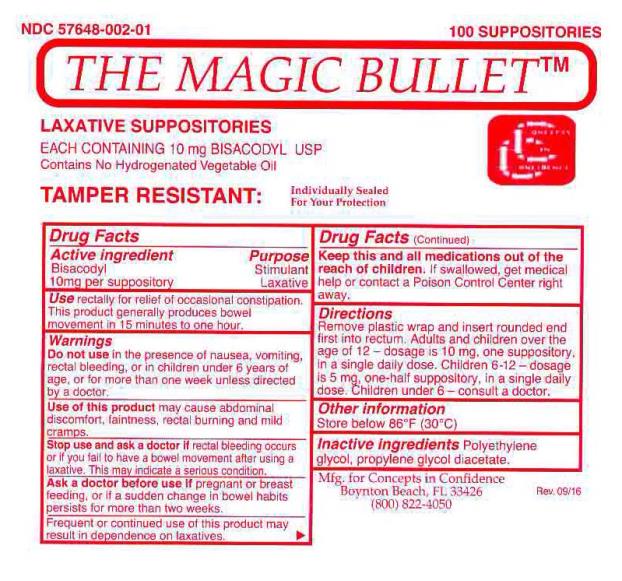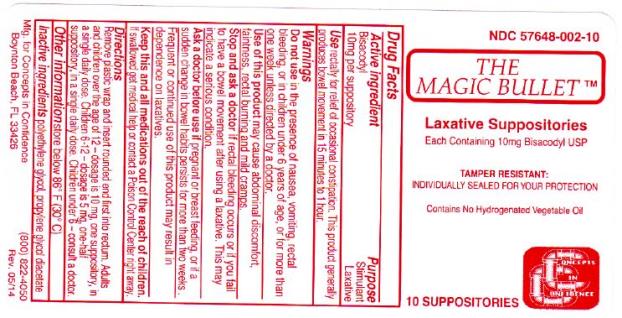 DRUG LABEL: The Magic Bullet
NDC: 57648-002 | Form: SUPPOSITORY
Manufacturer: Concepts in Confidence
Category: otc | Type: HUMAN OTC DRUG LABEL
Date: 20230404

ACTIVE INGREDIENTS: BISACODYL 10 mg/1 1
INACTIVE INGREDIENTS: POLYETHYLENE GLYCOL 1450; POLYETHYLENE GLYCOL 400; PROPYLENE GLYCOL DIACETATE

The Magic Bullet

DRUG FACTS

Active Ingredient

Bisacodyl
10 mg per suppository.

Purpose

Stimulant
Laxative

Use

rectally for relief of occasional constipation. This product generally produces a bowel movement within 15 minutes to one hour.

Warnings

Do not use

if presence nausea, vomiting, rectal bleeding, or in children under 5 years of age or for more than one week unless directed by a doctor.

Use of this product

may cause abdominal discomfort, faintness, rectal burning and mild cramps.

Stop use and ask a doctor If

rectal bleeding occurs or if you fail to have a bowel movement after using a laxative. This may indicate a serious condition.

Ask a doctor before use

If pregnant or breast feeding, or if a sudden change in bowel habits persists for more than two weeks.

Frequent or continued use of this product may result in dependence on laxatives.

DRUG FACTS (continued)

Keep this and all medication out of the reach of children.

If swallowed, get medical help or contact a Poison Control Center right away.

Directions

Remove plastic wrap and insert rounded end first into the rectum.

Adults and children over the age of 12 – dosage – 10 mg, one suppository, in a single daily dose. Children 6-12 – dosage – 5 mg, one-half suppository, in a single daily dose. Children under 6 – consult a doctor.

Other information

Store below 86°F (30°C)

Inactive ingredients

Polyethylene glycol, propylene glycol diacetate.

Mfg. for Concepts in Confidence

Boynton Beach, FL 33426

(800) 822-4050

Rev 09/16

DRUG FACTS

Active Ingredient

Bisacodyl
10 mg per suppository.

Purpose

Stimulant
Laxative

Use

rectally for relief of occasional constipation. This product generally produces a bowel movement within 15 minutes to one hour.

Warnings

Do not use

if presence nausea, vomiting, rectal bleeding, or in children under 5 years of age or for more than one week unless directed by a doctor.

Use of this product

may cause abdominal discomfort, faintness, rectal burning and mild cramps.

Stop use and ask a doctor If

rectal bleeding occurs or if you fail to have a bowel movement after using a laxative. This may indicate a serious condition.

Ask a doctor before use

If pregnant or breast feeding, or if a sudden change in bowel habits persists for more than two weeks.

Frequent or continued use of this product may result in dependence on laxatives.

DRUG FACTS (continued)

Keep this and all medication out of the reach of children.

If swallowed, get medical help or contact a Poison Control Center right away.

Directions

Remove plastic wrap and insert rounded end first into the rectum.

Adults and children over the age of 12 – dosage – 10 mg, one suppository, in a single daily dose. Children 6-12 – dosage – 5 mg, one-half suppository, in a single daily dose. Children under 6 – consult a doctor.

Other information

Store below 86°F (30°C)

Inactive ingredients

Polyethylene glycol, propylene glycol diacetate.

Mfg. for Concepts in Confidence

Boynton Beach, FL 33426

(800) 822-4050

Rev 05/14

PRINCIPAL DISPLAY PANEL – 100 Suppositories

NDC 57648-002-01

100 SUPPOSITORIES

THE MAGIC BULLET™

LAXATIVE SUPPOSITORIES

EACH CONTAINING 10 mg BISACODYL USP
Contains No Hydrogenated Vegetable Oil

TAMPER RESISTANT: Individually Sealed For Your Protection

PRINCIPAL DISPLAY PANEL – 10 Suppositories

NDC 57648-002-10

THE MAGIC BULLET™

LAXATIVE SUPPOSITORIES

EACH CONTAINING 10 mg BISACODYL USP

TAMPER RESISTANT:
INDIVIDUALLY SEALED FOR YOUR PROTECTION

Contains No Hydrogenated Vegetable Oil

10 SUPPOSITORIES

Concepts in Confidence